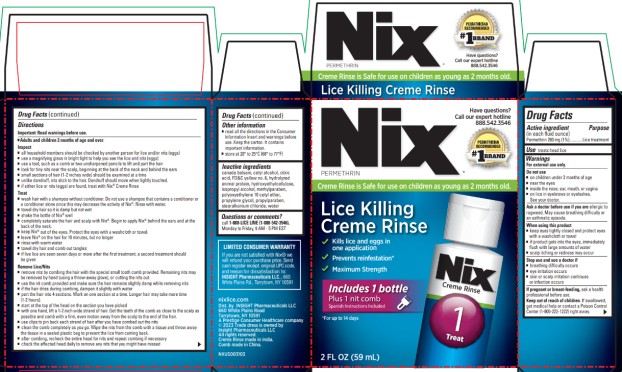 DRUG LABEL: Nix
NDC: 63736-030 | Form: RINSE
Manufacturer: Insight Pharmaceuticals LLC
Category: otc | Type: HUMAN OTC DRUG LABEL
Date: 20251023

ACTIVE INGREDIENTS: PERMETHRIN 1 g/100 mL
INACTIVE INGREDIENTS: CANADA BALSAM; CETYL ALCOHOL; CITRIC ACID MONOHYDRATE; FD&C YELLOW NO. 6; PROPYLENE GLYCOL; STEARALKONIUM CHLORIDE; WATER; ISOPROPYL ALCOHOL; METHYLPARABEN; PROPYLPARABEN

Nix Creme Rinse - 63736-030

Drug Facts

Active ingredient (in each fluid ounce)

Permethrin 280 mg (1%)

Purpose

Lice treatment

Use

treats head lice

Warnings

For external use only

Do not use

- on children under 2 months of age
- near the eyes
- inside the nose, ear, mouth, or vagina
- on lice in eyebrows or eyelashes. See your doctor.

Ask a doctor before use if you are

allergic to ragweed. May cause breathing difficulty or an asthmatic episode.

When using this product

- keep eyes tightly closed and protect eyes with a washcloth or towel
- if product gets into the eyes, immediately flush with large amounts of water
- scalp itching or redness may occur

Stop use and see a doctor if

- breathing difficulty occurs
- eye irritation occurs
- skin or scalp irritation continues or infection occurs

If pregnant or breast-feeding,

ask a health professional before use.

Keep out of reach of children.

If swallowed, get medical help or contact a Poison Control Center (1-800-222-1222) right away.

Directions

Important: Read warnings before use

■ Adults and children 2 months of age and over:

Inspect

- all household members should be checked by another person for lice and/or nits (eggs)
- use a magnifying glass in bright light to help you see the lice and nits (eggs)
- use a tool, such as a comb or two unsharpened pencils to lift and part the hair
- look for tiny nits near the scalp, beginning at the back of the neck and behind the ears
- small sections of hair (1-2 inches wide) should be examined at a time
- unlike dandruff, nits stick to the hair. Dandruff should move when lightly touched.
- if either lice or nits (eggs) are found, treat with Nix® Creme Rinse

Treat

- wash hair with a shampoo without conditioner. Do not use a shampoo that contains a conditioner or a conditioner alone since this may decrease the activity of Nix®. Rinse with water.
- towel dry hair so it is damp but not wet
- shake the bottle of Nix® well
- completely saturate the hair and scalp with Nix®. Begin to apply Nix® behind the ears and at the back of the neck.
- keep Nix® out of the eyes. Protect the eyes with a washcloth or towel.
- leave Nix® on the hair for 10 minutes, but no longer
- rinse with warm water
- towel dry hair and comb out tangles
- if live lice are seen seven days or more after the first treatment, a second treatment should be given

Remove Lice/Nits

- remove nits by combing the hair with the special small tooth comb provided. Remaining nits may be removed by hand (using a throw-away glove), or cutting the nits out.
- use the nit comb provided and make sure the hair remains slightly damp while removing nits
- if the hair dries during combing, dampen it slightly with water
- part the hair into 4 sections. Work on one section at a time. Longer hair may take more time (1-2 hours).
- start at the top of the head on the section you have picked
- with one hand, lift a 1-2 inch wide strand of hair. Get the teeth of the comb as close to the scalp as possible and comb with a firm, even motion away from the scalp to the end of the hair.
- use clips to pin back each strand of hair after you have combed out the nits
- clean the comb completely as you go. Wipe the nits from the comb with a tissue and throw away the tissue in a sealed plastic bag to prevent the lice from coming back.
- after combing, recheck the entire head for nits and repeat combing if necessary
- check the affected head daily to remove any nits that you might have missed

Other information

- read all the directions in the Consumer Information Insert and warnings before use. Keep the carton. It contains important information.
- store at 20° to 25°C (68° to 77°F)

Inactive ingredients

canada balsam, cetyl alcohol, citric acid, FD&C yellow no. 6, hydrolyzed animal protein, hydroxyethylcellulose, isopropyl alcohol, methylparaben, polyoxyethylene 10 cetyl ether, propylene glycol, propylparaben, stearalkonium chloride, water

Questions or comments?

Call 1-888-LICE LINE (1-888-542-3546).

Monday to Friday, 9AM-5PM EST

PRINCIPAL DISPLAY PANEL

Nix®
Lice Killing Creme Rinse

Includes 1 bottle

Plus 1 nit comb

Spanish instructions included

2 FL OZ (59 mL)